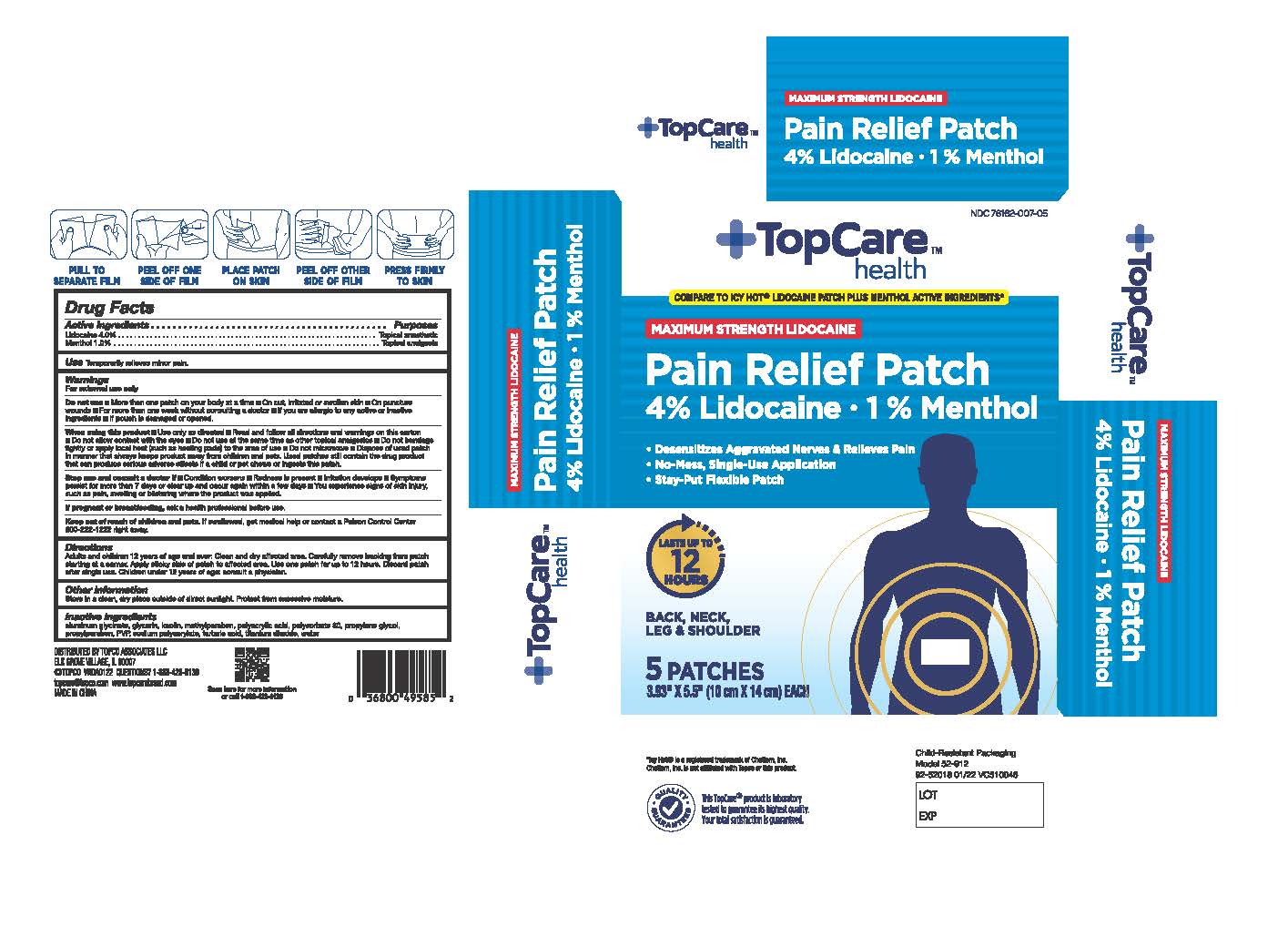 DRUG LABEL: TopCare Pain Relief Patch
NDC: 76162-007 | Form: PATCH
Manufacturer: Topco Associates LLC
Category: otc | Type: HUMAN OTC DRUG LABEL
Date: 20251228

ACTIVE INGREDIENTS: LIDOCAINE 4 g/100 g; MENTHOL, UNSPECIFIED FORM 1 g/100 g
INACTIVE INGREDIENTS: DIHYDROXYALUMINUM AMINOACETATE ANHYDROUS; SODIUM POLYACRYLATE (2500000 MW); POVIDONE, UNSPECIFIED; GLYCERIN; METHYLPARABEN; KAOLIN; POLYSORBATE 80; PROPYLENE GLYCOL; POLYACRYLIC ACID (250000 MW); TARTARIC ACID; TITANIUM DIOXIDE; PROPYLPARABEN; WATER

TopCare Pain Relief Patch Lidocaine plus Menthol

Active ingredients

Lidocaine 4%
Menthol 1%

Purposes

Topical anesthetic
Topical analgesic

Use

for the temporary relief of pain

Warnings

For external use only

Do not use

- more than 1 patch on your body at a time
- On cut, irritated, or swollen skin
- on puncture wounds
- For more than one week without consulting a doctor
- If you are allergic to any active or inactive ingredients
- if pouch is damaged or opened

When using this product

- use only as directed
- Read and follow all directions and warnings on this carton
- Do not allow contact with the eyes
- Do not use at the same time as other topical analgesics
- Do not bandage tightly or apply local heat (such as heating pads) to the area of use
- Do not microwave
- dispose of used patch in manner that always keeps product away from children and pets. Used patches still contain the drug product that can produce serious adverse effects if a child or pet chews or ingests this patch.

Stop use and ask a doctor if

- condition worsens
- Redness is present
- Irritation develops
- Symptoms persist for more than 7 days or clear up and occur again within a few days
- you experience signs of skin injury, such as pain, swelling, or blistering where the product was applied

If pregnant or breast-feeding,

ask a health professional before use.

Keep out of reach of children and pets.

If swallowed, get medical help or contact a Poison Control Center 800-222-1222 right away.

Directions

adults and children 12 years of age and over:

- clean and dry affected area
- carefully remove backing from patch starting at a corner.
- Appli sticky side of patch to affected area.
- Use one patch for up to 12 hours
- Dispatch patch after a single use.
- children under 12 years of age: consult a physician

Inactive ingredients

aluminum glycinate, glycerin, kaolin, methylparaben, polyacrylic acid, polysorbate 80, propylene glycol, propylparaben, PVP, sodium polyacrylate, tartaric acid, titanium dioxide, water.